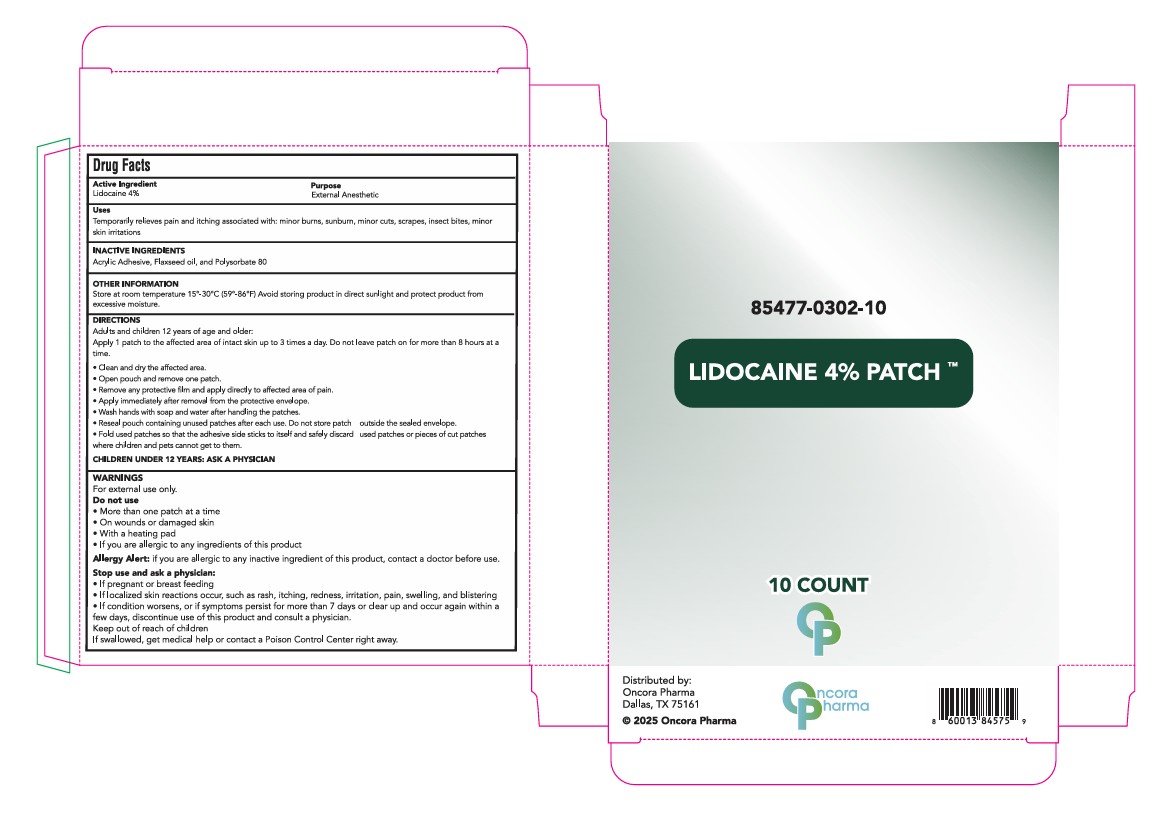 DRUG LABEL: Lidocaine 4% Patch
NDC: 85477-302 | Form: PATCH
Manufacturer: Oncora Pharma, LLC
Category: otc | Type: HUMAN OTC DRUG LABEL
Date: 20250627

ACTIVE INGREDIENTS: LIDOCAINE 40 mg/1 g
INACTIVE INGREDIENTS: FLAX SEED; POLYSORBATE 80; ACRYLIC ACID

Lidocaine 4% Topical Patch

Active Ingredients

Lidocaine 4%

Purpose

Topical Anesthetic

Uses

Temporarily relieves pain and itching associated with: minor burns, sunburn, minor cuts, scrapes, insect bites, minor skin irritations.

Warnings

For external use only

Do not use:

- More than 1 patch at a time
- On wounds or damaged skin
- With a heating pad
- If you are allergic to any ingredients of this product

When using this product:

- Use only as directed
- Avoid contact with the eyes, mucous membranes, or rashes
- Do not bandage tightly

Stop use and ask a doctor if:

- Localized skin reactions occur, such as rash, itching, redness, irritation, pain, swelling and blistering
- Conditions worsen
- Symptoms persist for more than 7 days
- Symptoms clear up and occur again within a few days

PREGNANCY OR BREAST FEEDING

If pregnant or breast-feeding,ask a health professional before use.

Keep out of reach of children.If swallowed, get medical help or contact a Poison Control Center right away.

Directions

Adults and children 12 years of age or over:

Apply 1 patch to the affected area of intact skin up to 3 times a day. Do not leave patch on for more than 8 hours at a time.

- Clean and dry the affected area
- Open pouch and remove one patch
- Remove any protective film and apply directly to affected area of pain
- Apply immediately after the removal of the protective envelope
- Wash hands with soap and water after handling the patches
- Reseal pouch containing unused patches after each use. Do not store patch outside the sealed envelope.
- Fold used patches so that the adhesive side sticks to itself and safely discard used patches or pieces of cut patches where children and pets cannot get to them.

Children under 12 years of age:Ask a physician

Other Information

Store at room temperature 15° - 30° C (59° - 86° F)

- Avoid storing product in direct sunlight
- Protect product from excessive moisture

Other Ingredients

Acrylic Adhesive, Flaxseed oil, and Polysorbate 80